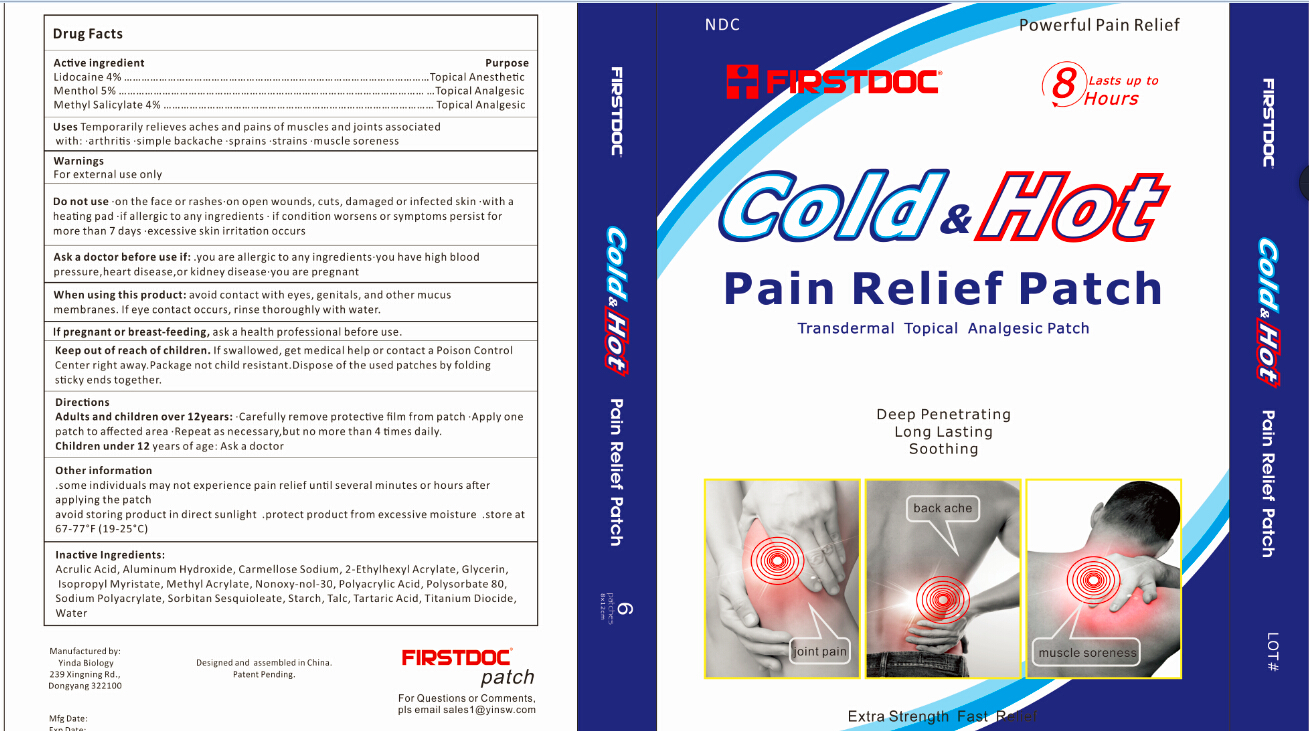 DRUG LABEL: PAIN RELIEF
NDC: 70355-001 | Form: PATCH
Manufacturer: ZHEJIANG DONGYANG YINDA BIOLOGY CO., LTD
Category: otc | Type: HUMAN OTC DRUG LABEL
Date: 20160106

ACTIVE INGREDIENTS: LIDOCAINE 4 g/100 g; METHYL SALICYLATE 4 g/100 g; MENTHOL 5 g/100 g
INACTIVE INGREDIENTS: WATER; TALC; TARTARIC ACID; STARCH, CORN; SORBITAN SESQUIOLEATE; ACRYLIC ACID; ALUMINUM HYDROXIDE; CARBOXYMETHYLCELLULOSE SODIUM; 2-ETHYLHEXYL ACRYLATE; GLYCERIN; ISOPROPYL MYRISTATE; METHYL ACRYLATE; SODIUM POLYACRYLATE (2500000 MW); NONOXYNOL-30; POLYACRYLIC ACID (8000 MW); POLYSORBATE 80; TITANIUM DIOXIDE

Active Ingredient

Lidocaine 4% ………………………………………………………………………………………………Topical Anesthetic

Menthol 5% …………………………………………………………………………………………… Topical Analgesic

Methyl Salicylate 4% ………………………………………………………………………………… Topical Analgesic

Purpose

Topical Anesthetic

Use

Temporarily relieves aches and pains of muscles and joints associated

with: ·arthritis ·simple backache ·sprains ·strains ·muscle soreness

Warnings

For external use only

Do not use ·on the face or rashes·on open wounds, cuts, damaged or infected skin ·with a heating pad ·if allergic to any ingredients · if condition worsens or symptoms persist for more than 7 days ·excessive skin irritation occurs

Ask a doctor before use if: .you are allergic to any ingredients ·you have high blood pressure,heart disease,or kidney disease ·you are pregnant

When using this product: avoid contact with eyes, genitals, and other mucus membranes. If eye contact occurs, rinse thoroughly with water.

If pregnant or breast-feeding, ask a health professional before use.

Keep out of reach of children. If swallowed, get medical help or contact a Poison Control Center right away.Package not child resistant.Dispose of the used patches by folding sticky ends together.

Directions

Adults and children over 12years: ·Carefully remove protective film from patch ·Apply one patch to affected area ·Repeat as necessary,but no more than 4 times daily.

Children under 12 years of age: Ask a doctor

Inactive Ingredients

Acrulic Acid, Aluminum Hydroxide, Carmellose Sodium, 2-Ethylhexyl Acrylate, Glycerin, Isopropyl Myristate, Methyl Acrylate, Nonoxy-nol-30, Polyacrylic Acid, Polysorbate 80, Sodium Polyacrylate, Sorbitan Sesquioleate, Starch, Talc, Tartaric Acid, Titanium Diocide, Water

Other information

.some individuals may not experience pain relief until several minutes or hours after applying the patch

avoid storing product in direct sunlight .protect product from excessive moisture .store at 67-77°F (19-25°C)